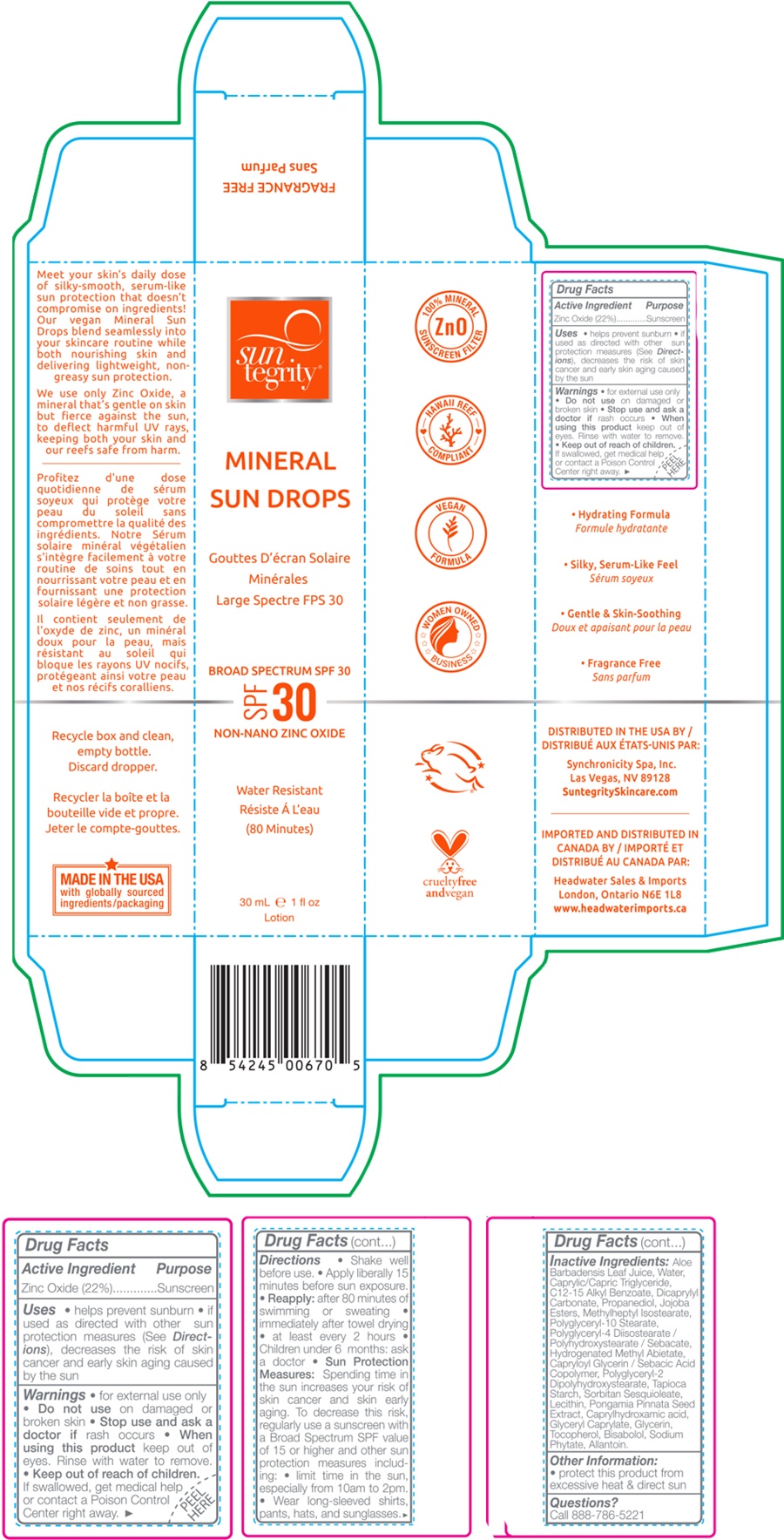 DRUG LABEL: Mineral Sun Drops
NDC: 69949-025 | Form: LOTION
Manufacturer: Synchronicity Spa, Inc. DBA Suntegrity
Category: otc | Type: HUMAN OTC DRUG LABEL
Date: 20251022

ACTIVE INGREDIENTS: Zinc Oxide 220 mg/1 mL
INACTIVE INGREDIENTS: ALOE VERA LEAF; WATER; MEDIUM-CHAIN TRIGLYCERIDES; ALKYL (C12-15) BENZOATE; DICAPRYLYL CARBONATE; PROPANEDIOL; POTASSIUM HYDROLYZED JOJOBA ESTERS; METHYLHEPTYL ISOSTEARATE; POLYGLYCERYL-10 STEARATE; POLYGLYCERYL-4 DIISOSTEARATE/POLYHYDROXYSTEARATE/SEBACATE; HYDROGENATED METHYL ABIETATE; CAPRYLOYL GLYCERIN/SEBACIC ACID COPOLYMER (2000 MPA.S); POLYGLYCERYL-2 DIPOLYHYDROXYSTEARATE; STARCH, TAPIOCA; SORBITAN SESQUIOLEATE; SOYBEAN LECITHIN; PONGAMOL; TOCOPHEROL; .ALPHA.-BISABOLOL, (+/-)-; CAPRYLHYDROXAMIC ACID; GLYCERYL MONOCAPRYLATE; GLYCERIN; PHYTATE SODIUM; ALLANTOIN

Mineral Sun Drops

Drug Facts

Active Ingredient

Zinc Oxide 22%

Purpose

Sunscreen

Uses

- Helps prevent sunburn
- If used as directed with other sun protection measures (see Directions), decreases the risk of skin cancer and early skin aging caused by the sun.

Warnings

- For external use only

- Do not use on damaged or broken skin

- Stop use and ask a doctor if rash occurs

- When using this product keep out of eyes. Rinse with water to remove.

- Keep out of reach of children. If swallowed, get medical help or contact a Poison Control Center right away.

Directions

- Shake well before use.
- Apply liberally 15 minutes before sun exposure.
- Reapply: after 80 minutes of swimming or sweating; immediately after towel drying; at least every 2 hours
- Children under 6 months: ask a doctor.
- Sun Protection Measures: Spending time in the sun increases your risk of skin cancer and skin early aging. To decrease this risk, regularly use a sunscreen with a Broad Spectrum SPF value of 15 or higher and other sun protection measures including: - limit time in the sun, expecially from 10am to 2pm – Wear long-sleeved shirts, pants, hats, and sunglasses.

Inactive Ingredients

Aloe Barbadensis Leaf Juice and Water, Caprylic/Capric Triglyceride, C12-15 Alkyl Benzoate, Dicaprylyl Carbonate, Propanediol, Jojoba Esters, Methylheptyl Isostearate, Polyglyceryl-10 Stearate, Polyglyceryl-4 Diisostearate/Polyhydroxystearate/Sebacate, Hydrogenated Methyl Abietate, Caprylol Glycerin/Sebacic Acid Copolymer, Polyglyceryl-2 Dipolyhydroxystearate, Caprylhydroxamic acid (and) Glyceryl Caprylate (and) Glycerin, Tapioca Starch, Sorbitan Sesquioleate, Lecithin, Pongamia Pinnata Seed Extract, Tocopherol, Bisabolol, Sodium Phytate, Allantoin.

Other Information

Protect this product from excessive heat & direct sun

Questions?

Call 888-786-5221

DISTRIBUTED BY:
Synchronicity Spa, Inc.
Las Vegas, NV 89128

PRINCIPAL DISPLAY PANEL - 30 mL Bottle Box

sun
tegrity®

MINERAL
SUN DROPS

BROAD SPECTRUM SPF 30
SPF 30
NON-NANO ZINC OXIDE

Water Resistant
(80 Minutes)

30 mL ℮ 1 fl oz
Lotion